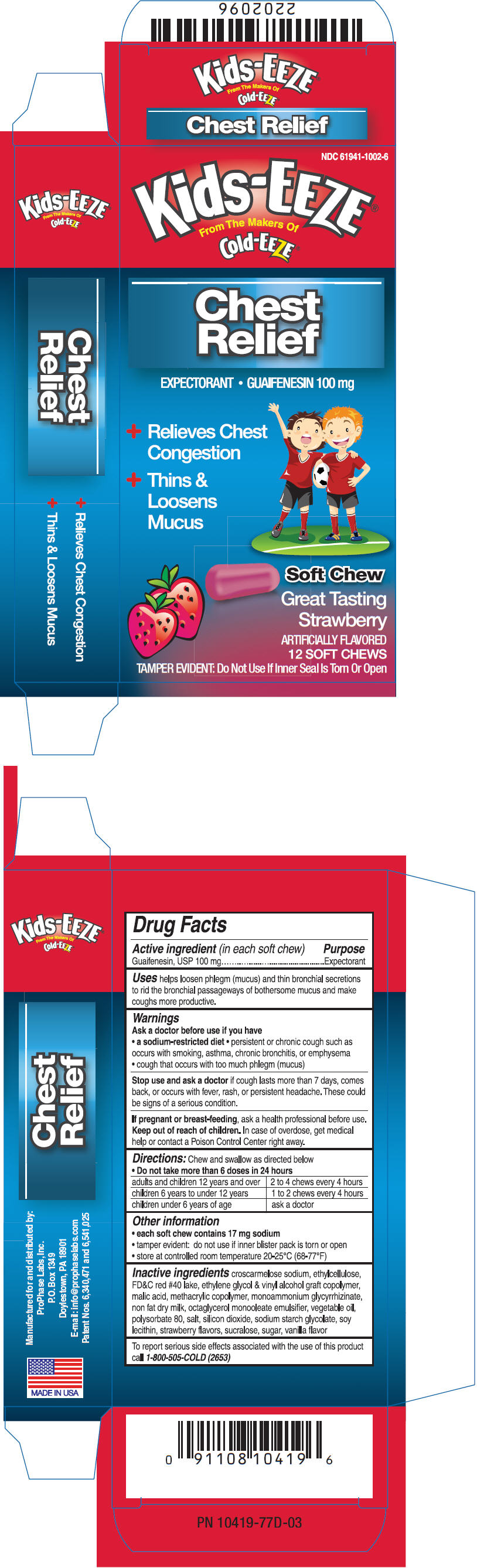 DRUG LABEL: Kids-EEZE 
NDC: 61941-1002 | Form: TABLET, ORALLY DISINTEGRATING
Manufacturer: ProPhase Labs, Inc.
Category: otc | Type: HUMAN OTC DRUG LABEL
Date: 20110401

ACTIVE INGREDIENTS: Guaifenesin 100 mg/1 1
INACTIVE INGREDIENTS: CROSCARMELLOSE SODIUM; ETHYLCELLULOSE (4 MPA.S); ETHYLENE GLYCOL; MALIC ACID; LECITHIN, SOYBEAN; METHACRYLIC ACID - METHYL METHACRYLATE COPOLYMER (1:2); SUCRALOSE; SODIUM STARCH GLYCOLATE TYPE A POTATO; SILICON DIOXIDE

Kids-EEZE®
Chest Relief

Drug Facts

Active ingredient (in each soft chew)

Guaifenesin, USP 100 mg

Purpose

Expectorant

Uses

helps loosen phlegm (mucus) and thin bronchial secretions to rid the bronchial passageways of bothersome mucus and make coughs more productive.

Warnings

Ask a doctor before use if you have

- a sodium-restricted diet
- persistent or chronic cough such as occurs with smoking, asthma, chronic bronchitis, or emphysema
- cough that occurs with too much phlegm (mucus)

Stop use and ask a doctor if cough lasts more than 7 days, comes back, or occurs with fever, rash, or persistent headache. These could be signs of a serious condition.

PREGNANCY OR BREAST FEEDING

If pregnant or breast-feeding, ask a health professional before use.

Keep out of reach of children. In case of overdose, get medical help or contact a Poison Control Center right away.

Directions

Chew and swallow as directed below

- Do not take more than 6 doses in 24 hours

adults and children 12 years and over | 2 to 4 chews every 4 hours
children 6 years to under 12 years | 1 to 2 chews every 4 hours
children under 6 years of age | ask a doctor

Other information

- each soft chew contains 17 mg sodium
- tamper evident: do not use if inner blister pack is torn or open
- store at controlled room temperature 20-25°C (68-77°F)

Inactive ingredients

croscarmelose sodium, ethylcellulose, FD&C red #40 lake, ethylene glycol & vinyl alcohol graft copolymer, malic acid, methacrylic copolymer, monoammonium glycyrrhizinate, non fat dry milk, octaglycerol monooleate emulsifier, vegetable oil, polysorbate 80, salt, silicon dioxide, sodium starch glycolate, soy lecithin, strawberry flavors, sucralose, sugar, vanilla flavor

QUESTIONS

To report serious side effects associated with the use of this product call 1-800-505-COLD (2653)

PRINCIPAL DISPLAY PANEL - 100 mg Tablet Carton

NDC 61941-1002-6

Kids-EEZE®

From The Makers Of
Cold-EEZE®

Chest
Relief

EXPECTORANT • GUAIFENESIN 100 mg

+ Relieves Chest
  Congestion
+ Thins &
  Loosens
  Mucus

Soft Chew

Great Tasting
Strawberry

ARTIFICIALLY FLAVORED
12 SOFT CHEWS

TAMPER EVIDENT: Do Not Use If Inner Seal Is Torn Or Open